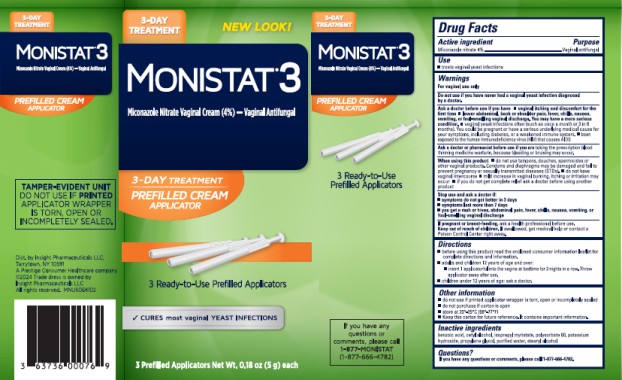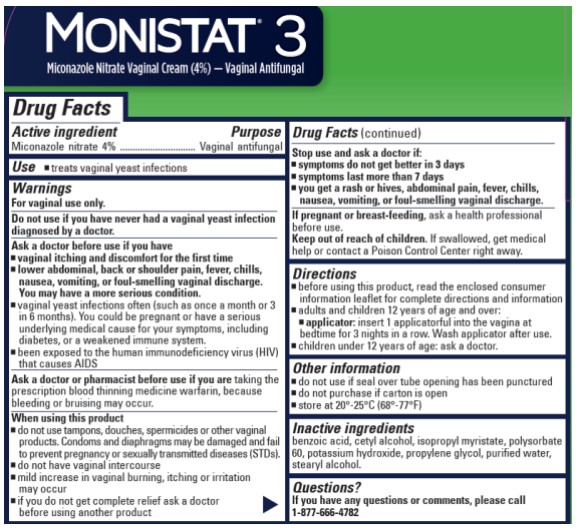 DRUG LABEL: Monistat 3
NDC: 63736-015 | Form: CREAM
Manufacturer: Insight Pharmaceuticals LLC
Category: otc | Type: HUMAN OTC DRUG LABEL
Date: 20251023

ACTIVE INGREDIENTS: Miconazole Nitrate 40 mg/1 g
INACTIVE INGREDIENTS: Benzoic Acid; Cetyl Alcohol; Isopropyl Myristate; Polysorbate 60; Potassium Hydroxide; Propylene Glycol; Water; Stearyl Alcohol

Monistat 3 3 Day 63736-015

Drug Facts

Active ingredient

Miconazole nitrate 4%

Purpose

Vaginal antifungal

Use

- treats vaginal yeast infections

Warnings

For vaginal use only

Do not use if

you have never had a vaginal yeast infection diagnosed by a doctor.

Ask a doctor before use if you have

- vaginal itching and discomfort for the first time
- lower abdominal, back or shoulder pain, fever, chills, nausea, vomiting, or foul-smelling vaginal discharge. You may have a more serious condition.
- vaginal yeast infections often (such as once a month or 3 in 6 months). You could be pregnant or have a serious underlying medical cause for your symptoms, including diabetes or a weakened immune system.
- been exposed to human immunodeficiency virus (HIV) that causes AIDS

Ask a doctor or pharmacist before use if you are

taking the prescription blood thinning medicine warfarin, because bleeding or bruising may occur

When using this product

- do not use tampons, douches, spermicides, or other vaginal products. Condoms and diaphragms may be damaged and fail to prevent pregnancy or sexually transmitted disease (STDs).
- do not have vaginal intercourse
- mild increase in vaginal burning, itching, or irritation may occur
- if you do not get complete relief ask a doctor before using another product

Stop use and ask a doctor if

- symptoms do not get better after 3 days
- symptoms last more than 7 days
- you get a rash or hives, abdominal pain, fever, chills, nausea, vomiting, or foul-smelling vaginal discharge

If pregnant or breast feeding,

ask a health professional before use.

Keep out of reach of children.

If swallowed, get medical help or contact a Poison Control Center right away.

Directions

- before using this product read the enclosed consumer information leaflet for complete directions and information
- adults and children 12 years of age and over:
  ▪ insert 1 applicatorful into the vagina at bedtime for 3 nights in a row. Throw applicator away after use.
- children under 12 years of age: ask a doctor

Other information

- do not use if printed applicator wrapper is torn, open or incompletely sealed
- do not purchase if carton is open
- store at 20° - 25°C (68° - 77°F)
- Keep this carton for future reference. It contains important information.

Inactive ingredients

benzoic acid, cetyl alcohol, isopropyl myristate, polysorbate 60, potassium hydroxide, propylene glycol, purified water, stearyl alcohol

Questions?

If you have any questions or comments, please call 1-877-666-4782

PRINCIPAL DISPLAY PANEL - 5 g Tube Carton

3-DAY TREATMENT

Prefilled Cream Applicator

MONISTAT® 3
Miconazole Nitrate Vaginal Cream (4%)- Vaginal Antifungal

3 Prefilled Applicators Net Wt. 0.18 oz. (5g) each